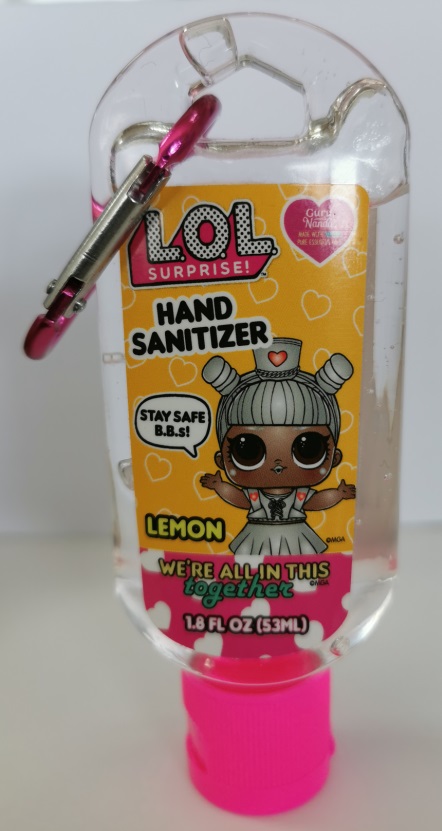 DRUG LABEL: Hand Sanitizer LOL
NDC: 70708-073 | Form: GEL
Manufacturer: GURUNANDA LLC
Category: otc | Type: HUMAN OTC DRUG LABEL
Date: 20220831

ACTIVE INGREDIENTS: ALCOHOL 70 mL/100 mL
INACTIVE INGREDIENTS: AMINOMETHYL PROPANEDIOL 0.2 mL/100 mL; CARBOMER 940 0.5 mg/100 mL; WATER 25.089 mL/100 mL; HYDROGENATED CASTOR OIL 2 mL/100 mL; SODIUM TRIETHANOLAMINE TRIS(DIHYDROGEN PHOSPHATE) 0.01 mg/100 mL; DEANOL 0.001 mL/100 mL; GLYCERIN 1.2 mg/100 mL; CITRUS LIMON FRUIT OIL 1 mL/100 mL

Hand Sanitizer LOL -1.8 fl. oz

ACTIVE INGREDIENT

Ethyl Alcohol 70% v/v

PURPOSE

Antiseptic

WARNINGS

FOR EXTERNAL USE ONLY

When using this product do not use in or near the eyes, mouth or open skin wounds. In case of contact, rinse the area thoroughly with water.

Stop use and ask a doctor if irritation or rash appears and lasts for more than 72 hours.

Keep out of reach of children. If swallowed, get medical help or contact a Poison Control Center right away. Poison Control can be reached at (800) 222-1222

DOSAGE AND ADMINISTRATION

-Place enough product on hands to cover all surfaces. Rub hands together until dry.

-Supervise children under 6 years when using this product to avoid swallowing.

- Not intended for children under 2 years.

OTHER SAFETY INFORMATION

Store below 110° F (43° C)

INDICATIONS AND USAGE

Helps to reduce bacteria on skin

INACTIVE INGREDIENT

Water, Peg-40 (Hydrogenated Castor Oil), Glycerin, Lemon (Citrus Limon), Carbomer, Aminomethyl Propanol, Triethanolamine, 2-Dimethylaminoethanol